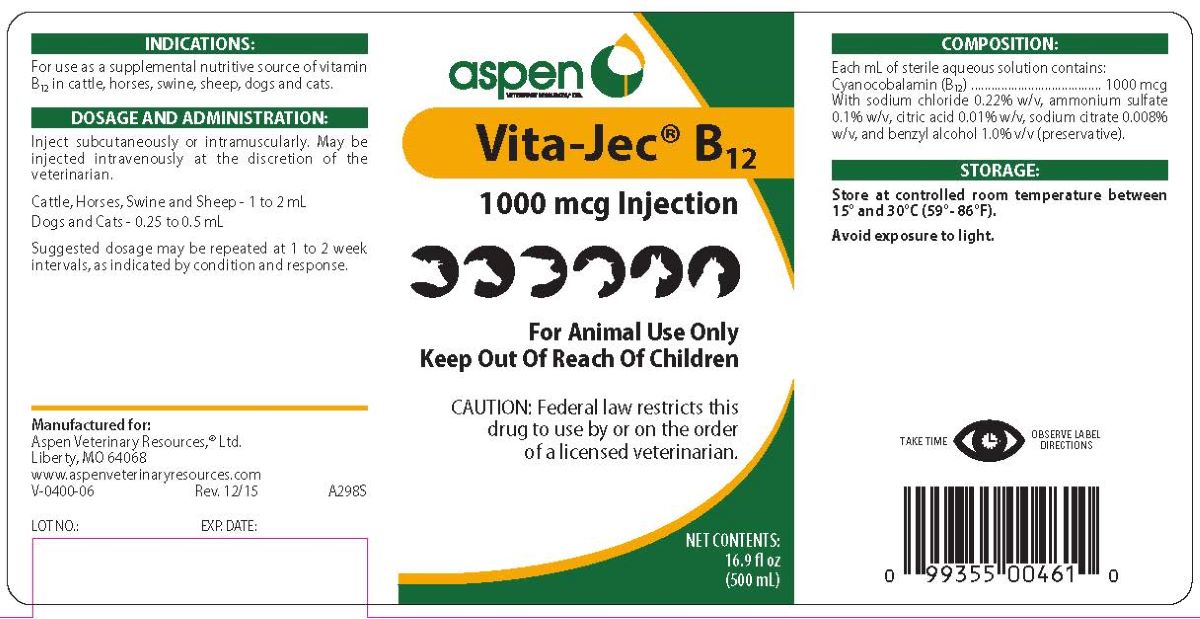 DRUG LABEL: VITA-JEC B12  1000
NDC: 46066-202 | Form: INJECTION
Manufacturer: Aspen Veterinary Resources, Ltd
Category: animal | Type: PRESCRIPTION ANIMAL DRUG LABEL
Date: 20251022

ACTIVE INGREDIENTS: CYANOCOBALAMIN 1000 ug/1 mL
INACTIVE INGREDIENTS: WATER

VITAMIN B12 INJECTION

INDICATIONS

For use as a supplemental nutritive source of vitamin B12 in cattle, horses, swine, sheep, dogs and cats.

DOSAGE AND ADMINISTRATION

Inject subcutaneously or intramuscularly. May be injected intravenously at the discretion of the veterinarian.

Cattle, Horses, Swine and Sheep--1 to 2 mL.
Dogs and Cats--0.25 to 0.5 mL.

Suggested dosage may be repeated at 1 to 2 week intervals, as indicated by condition and response.

TAKE TIME OBSERVE LABEL DIRECTIONS

COMPOSITION

Each mL of sterile aqueous solution contains:
Cyanocobalamin (B12) 1000 mcg with sodium chloride 0.22% w/v, ammonium sulfate 0.1% w/v, citric acid 0.01% w/v, sodium citrate 0.008% w/v, and benzyl alcohol 1.0% v/v (preservative).

STORAGE AND HANDLING

Store at controlled room temperature between 15o to 30oC (59o - 86oF).

Avoid exposure to light.

PACKAGE LABEL

FOR ANIMAL USE ONLY

KEEP OUT OF REACH OF CHILDREN

Caution: Federal law restricts this drug to use by or on the order of a licensed veterinarian.

NET CONTENTS